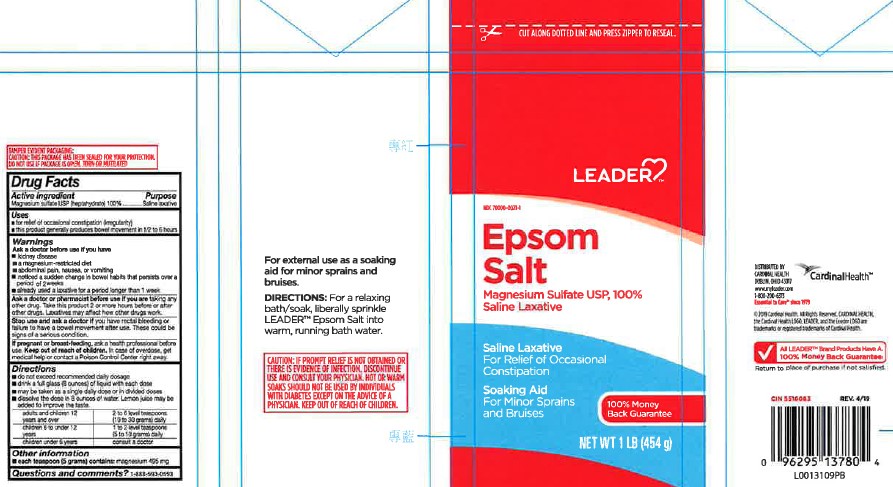 DRUG LABEL: Epsom Salt
NDC: 70000-0021 | Form: CRYSTAL
Manufacturer: Cardinal Health, 110 dba Leader
Category: otc | Type: HUMAN OTC DRUG LABEL
Date: 20260129

ACTIVE INGREDIENTS: MAGNESIUM SULFATE HEPTAHYDRATE 1 g/1 g

Leader 602.002/602AA
Epsom Salt

Tamper Evident Statement

TAMPER EVIDENT PACKAGING:

CAUTION: THIS PACKAGE HAS BEEN SEALED FOR YOUR PROTECTION.

DO NOT USE IF PACKAGE IS OPEN, TORN OR MUTILATED

Active ingredient

Magnesium sulfate USP (heptahydrate)100%

Purpose

Saline Laxative

Uses

- for relief of occasional constipation (irregularity)
- this product generally produces bowel movement in 1/2 to 6 hours

Warning

for this product

Ask a doctor before use if you have

- kidney disease
- a magnesium-restricted diet
- abdominal pain, nausea, or vomiting
- noticed a sudden change in bowel habits that persists over a period of 2 weeks
- already used a laxative for a period longer than 1 week

Ask a doctor or pharmacist before use if you are

taking any other drug. Take this product 2 or more hours before or after other drugs. Laxatives may affect how other drugs work.

Stop use and ask a doctor if

you have rectal bleeding or failure to have a bowel movement after use. These could be signs of a serious condition.

If pregnant or breast-feeding,

ask a health professional before use.

Keep out of reach of children.

In case of overdose, get medical help or contact a Poison Control Center right away.

Directions

- do not exceed recommended daily dosage
- drink a full glass (8 ounces) of liquid with each dose
- may be taken as a single daily dose or in divided doses
- dissolve the dose in 8 ounces of water. Lemon juice may be added to improve the taste.

adults and children 12 years and over - 2 to 6 level teaspoons (10 to 30 grams) daily

children 6 to under 12 years - 1 to 2 level teaspoons (5 to 10 grams) daily

children under 6 years - consult a doctor

Other information

- each teaspoon (5 grams) contains: magnesium 495 mg

Questions and comments?

1-888-593-0593

claims

For external use as a soaking aid for minor sprains and bruises.

Directions: For a relaxing bath/soak, liberally sprinkle LEADER™ Epsom Salt into warm, running bath water

Caution: IF PROMPT RELIEF IS NOT OBTAINED OR THERE IS EVIDENCE OF INFECTION, DISCONTINUE USE AND CONSULT YOUR PHYSICIAN. HOT OR WARM SOAKS SHOULD NOT BE USED BY INDIVIDUALS WITH DIABETES EXCEPT ON THE ADVICE OF A PHYSICIAN. KEEP OUT OF REACH OF CHILDREN.

Inactive Ingredient

None

Adverse reactions section

Cardinal Health™

DISTRIBUTED BY

CARDINAL HEALTH

DUBLIN, OHIO 43017

www.myleader.com

1-800-200-6313

Essential to Care since 1979

©2019 Cardinal Health. All Rights Reserved. CARDINAL HEALTH, the Cardinal Health LOGO, LEADER and the Leader LOGO are trademarks or registered trademarks of Cardinal Health.

ALL LEADER™ Brand Product Have A 100% Money Back Guarantee

Return to place of purchase if not satisfied.

CIN 5516083 REV 4/19

principal display panel

CUT ALONG DOTTED LINE AND PRESS ZIPPER TO RESEAL

LEADER™

NDC 70000-0021-1

EPSOM

SALT

Magnesium Sulfate USP, 100%

Saline Laxative

Saine Laxative

For Relief of Occasional Constipation

Soaking Aid

For Minor Sprains and Bruises

100% Money Back Guarantee

Net WT 1 LB (454 g)